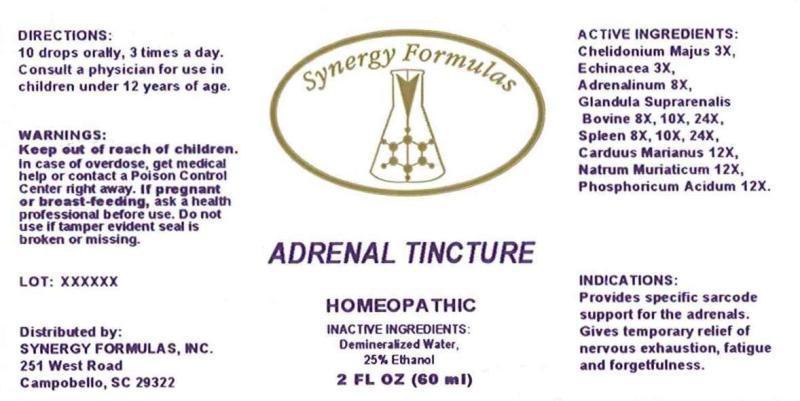 DRUG LABEL: Adrenal Tincture
NDC: 43772-0045 | Form: LIQUID
Manufacturer: Synergy Formulas, Inc.
Category: homeopathic | Type: HUMAN OTC DRUG LABEL
Date: 20150202

ACTIVE INGREDIENTS: CHELIDONIUM MAJUS 3 [hp_X]/1 mL; ECHINACEA ANGUSTIFOLIA 3 [hp_X]/1 mL; EPINEPHRINE 8 [hp_X]/1 mL; BOS TAURUS ADRENAL GLAND 8 [hp_X]/1 mL; BOS TAURUS SPLEEN 8 [hp_X]/1 mL; MILK THISTLE 12 [hp_X]/1 mL; SODIUM CHLORIDE 12 [hp_X]/1 mL; PHOSPHORIC ACID 12 [hp_X]/1 mL
INACTIVE INGREDIENTS: WATER; ALCOHOL

DRUG FACTS:

ACTIVE INGREDIENTS:

Chelidonium Majus 3X, Echinacea (Angustifolia) 3X, Adrenalinum 8X, Glandula Suprarenalis Bovine 8X, 10X, 24X, Spleen (Bovine) 8X, 10X, 24X, Carduus Marianus 12X, Natrum Muriaticum 12X, Phosphoricum Acidum 12X

INDICATIONS:

Provides specific sarcode support for the adrenals. Gives temporary relief of nervous exhaustion, fatigue and forgetfulness.

WARNINGS:

Keep out of reach of children. In case of overdose, get medical help or contact a Poison Control Center right away.

If pregnant or breast-feeding, ask a health professional before use.

Do not use if tamper evident seal is broken or missing.

Keep out of reach of children. In case of overdose, get medical help or contact a Poison Control Center right away.

DIRECTIONS:

10 drops orally, 3 times a day. Consult a physician for use in children under 12 years of age.

INDICATIONS:

Provides specific sarcode support for the adrenals. Gives temporary relief of nervous exhaustion, fatigue and forgetfulness.

INACTIVE INGREDIENTS:

Demineralized Water, 25% Ethanol

QUESTIONS:

Distributed by:

SYNERGY FORMULAS, INC

251 West Road

Campobello, SC 29322

PACKAGE LABEL DISPLAY:

Synergy Formulas

ADRENAL TINCTURE

HOMEOPATHIC

2 FL OZ (60 ml)